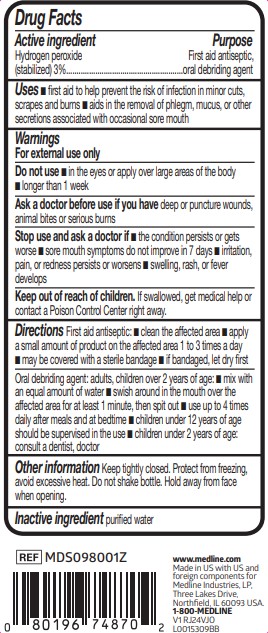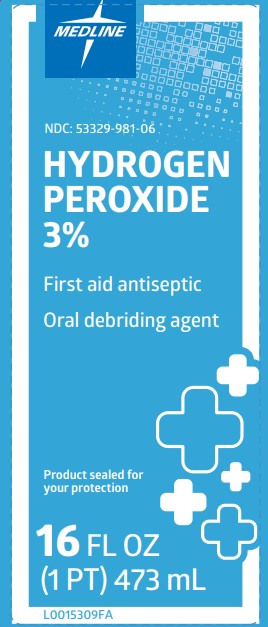 DRUG LABEL: Hydrogen Peroxide
NDC: 53329-981 | Form: LIQUID
Manufacturer: Medline Industries, LP
Category: otc | Type: HUMAN OTC DRUG LABEL
Date: 20260211

ACTIVE INGREDIENTS: HYDROGEN PEROXIDE 3 mL/100 mL
INACTIVE INGREDIENTS: WATER

981 Medline Hydrogen Peroxide Solution

Active ingredient

Hydrogen peroxide (stabilized) 3%

Purpose

First Aid Antiseptic
Oral debriding agent

Uses

- first aid to help prevent the risk of infection in minor cuts, scrapes and burns
- aids in the removal of phlegm, mucus, or other secretions associated with occasional sore mouth

Warnings

For external use only.

Do not use

- in the eyes or apply over large areas of the body
- longer than 1 week

Ask a doctor before use if you have

deep or puncture wounds, animal bites, or serious burns

Stop use and ask a doctor if

- condition persists or gets worse
- sore mouth symptoms do not improve in 7 days
- irritation, pain, or redness persists or worsens
- swelling, rash, or fever develops

Keep out of reach of children.

If swallowed, get medical help or contact a Poison Control Center right away.

Directions

First aid antiseptic:

- Clean the affected area
- Apply a small amount of product on the area 1 to 3 times a day
- May be covered with a sterile bandage
- If bandaged, let dry first

Oral debriding agent: adults, children over 2 years of age:

- mix with an equal amount of water
- swish around in the mouth over the affected area for at least 1 minute, then spit out
- use up to 4 times daily after meals and at bedtime
- children under 12 years of age should be supervised in the use
- children under 2 years of age: consult a dentist, doctor

Other information

Keep tightly closed. Protect from freezing, avoid excessive heat. Do not shake bottle. Hold away from face when opening.

Inactive ingredients

purified water

Manufacturing Information

www.medline.com

Made in US with US and foreign components

for Medline Industries, LP,
Three Lakes Drive, Northfield, IL 60093 USA
1-800-MEDLINE

REF: MDS098001Z